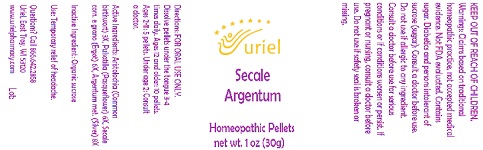 DRUG LABEL: Secale Argentum
NDC: 48951-8383 | Form: PELLET
Manufacturer: Uriel Pharmacy Inc.
Category: homeopathic | Type: HUMAN OTC DRUG LABEL
Date: 20210803

ACTIVE INGREDIENTS: PULSATILLA VULGARIS 6 [hp_X]/1 1; ARISTOLOCHIA CLEMATITIS WHOLE 3 [hp_X]/1 1; CLAVICEPS PURPUREA SCLEROTIUM 6 [hp_X]/1 1; SILVER 8 [hp_X]/1 1
INACTIVE INGREDIENTS: SUCROSE

Secale Argentum

INDICATIONS AND USAGE

Directions: FOR ORAL USE ONLY.

DOSAGE AND ADMINISTRATION

Directions: FOR ORAL USE ONLY.

ACTIVE INGREDIENT

Active Ingredients: Aristolochia (Common birthwort) 3X, Pulsatilla (Pasqueflower) 6X, Secale corn. e grano (Ergot) 6X, Argentum met. (Silver) 8X

Inactive Ingredient: Organic sucrose

PURPOSE

Use: Temporary relief of headache.

KEEP OUT OF REACH OF CHILDREN.

WARNINGS

Warnings: Claims based on traditional homeopathic practice, not accepted medical evidence. Not FDA evaluated. Contains sugar. Diabetics and persons intolerant of sucrose (sugar): Consult a doctor before use. Do not use if allergic to any ingredient. Consult a doctor before use for serious conditions or if conditions worsen or persist. If pregnant or nursing, consult a doctor before use. Do not use if safety seal is broken or missing.

Questions? Call 866.642.2858
Uriel, East Troy, WI 53120
www.urielpharmacy.com Lot: